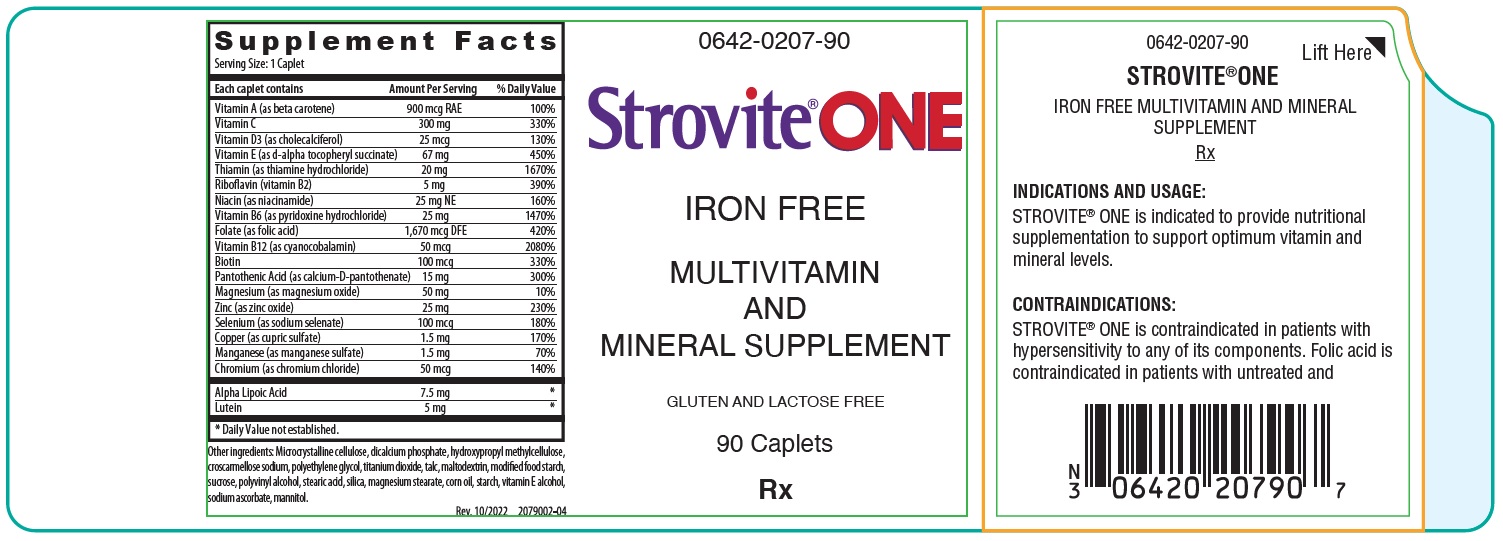 DRUG LABEL: Strovite One
NDC: 0642-0207 | Form: TABLET
Manufacturer: Exeltis USA, Inc.
Category: prescription | Type: HUMAN PRESCRIPTION DRUG LABEL
Date: 20250320

ACTIVE INGREDIENTS: MANGANESE 1.5 mg/1 1; VITAMIN A 900 ug/1 1; CALCIUM PANTOTHENATE 7.5 mg/1 1; ASCORBIC ACID 300 mg/1 1; CHOLECALCIFEROL 25 ug/1 1; .ALPHA.-TOCOPHEROL SUCCINATE, D- 45 ug/1 1; THIAMINE 20 mg/1 1; RIBOFLAVIN 5 mg/1 1; NIACINAMIDE 25 mg/1 1; PYRIDOXINE HYDROCHLORIDE 25 mg/1 1; FOLIC ACID 1700 ug/1 1; BIOTIN 100 ug/1 1; CYANOCOBALAMIN 50 ug/1 1; SELENIUM 100 ug/1 1; MAGNESIUM OXIDE 50 mg/1 1; ZINC OXIDE 25 mg/1 1; CUPRIC SULFATE 1.5 mg/1 1; CHROMIUM 50 ug/1 1; ALPHA LIPOIC ACID 15 mg/1 1; LUTEIN 5 mg/1 1
INACTIVE INGREDIENTS: HYDROXYPROPYL METHYLCELLULOSE; MALTODEXTRIN; STEARIC ACID; MANNITOL; CROSCARMELLOSE SODIUM; MICROCRYSTALLINE CELLULOSE; SILICON DIOXIDE; TITANIUM DIOXIDE; MAGNESIUM STEARATE; POLYVINYL ALCOHOL, UNSPECIFIED; STARCH, CORN; TALC; SUCROSE; POLYETHYLENE GLYCOL, UNSPECIFIED; ANHYDROUS DIBASIC CALCIUM PHOSPHATE; TOCOPHEROL; SODIUM ASCORBATE; .ALPHA.-TOCOPHEROL, DL-; MODIFIED CORN STARCH (1-OCTENYL SUCCINIC ANHYDRIDE); CORN OIL

STROVITE® ONE

0642-0207-90

STROVITE® ONE

IRON FREE MULTIVITAMIN AND MINERAL
SUPPLEMENT
Rx

COMPOSITION

Each caplet contains:
Vitamin A (as beta carotene) |  | 900 mcg RAE
Vitamin C |  | 300 mg
Vitamin D (as cholecalciferol) |  | 25 mcg
Vitamin E (as d-alpha tocopheryl succinate) |  | 67 mg
Thiamin (as thiamine hydrochloride) |  | 20 mg
Riboflavin (vitamin B2) |  | 5 mg
Niacin (as niacinamide) |  | 25 mg NE
Vitamin B6 (as pyridoxine hydrochloride) |  | 25 mg
Folate (as folic acid) |  | 1,670 mcg DFE
Vitamin B12 (as cyanocobalamin) |  | 50 mcg
Biotin |  | 100 mcg
Pantothenic Acid (as calcium-D-pantothenate) |  | 15 mg
Magnesium (as magnesium oxide) |  | 50 mg
Zinc (as zinc oxide) |  | 25 mg
Selenium (as sodium selenate) |  | 100 mcg
Copper (as cupric sulfate) |  | 1.5 mg
Manganese (as manganese sulfate) |  | 1.5 mg
Chromium (as chromium chloride) |  | 50 mcg
Alpha Lipoic Acid |  | 7.5 mg
Lutein |  | 5 mg

Other ingredients: Microcrystalline cellulose, dicalcium phosphate, hydroxypropyl methylcellulose, croscarmellose sodium, polyethylene glycol, titanium dioxide, talc, maltodextrin, modified food starch, sucrose, polyvinyl alcohol, stearic acid, silica, magnesium stearate, corn oil, starch, vitamin E alcohol, sodium ascorbate, mannitol.

INDICATIONS AND USAGE

STROVITE® ONE is indicated to provide nutritional supplementation to support optimum vitamin and mineral levels.

CONTRAINDICATIONS

STROVITE® ONE is contraindicated in patients with hypersensitivity to any of its components. Folic Acid is contraindicated in patients with untreated and uncomplicated pernicious anemia, and in those with anaphylactic sensitivity to folic acid.

Cyanocobalamin is contraindicated in patients with sensitivity to cobalt or to cyanocobalamin (Vitamin B12).

WARNING/PRECAUTIONS

Vitamin D supplementation should be used with caution in those with hypercalcemia or conditions that may lead to hypercalcemia such as hyperparathyroidism and those who form calcium-containing kidney stones. High doses of vitamin D can lead to elevated levels of calcium that reside in the blood and soft tissues. Bone pain, high blood pressure, formation of kidney stones, renal failure, and increased risk of heart disease can occur.

Folic acid, especially in doses above 0.1 mg daily, may obscure pernicious anemia, in that hematologic remission may occur while neurological manifestations remain progressive.

The use of folic acid doses above 1 mg daily may precipitate or exacerbate the neurological damage of vitamin B12 deficiency.

Avoid overdosage. Keep out of the reach of children.

PRECAUTIONS

Drug Interactions

High doses of folic acid may result in decreased serum levels of anticonvulsant drugs.

Vitamin D supplementation should not be given with large amounts of calcium in those with hypercalcemia or conditions that may lead to hyper-calcemia such as hyperparathyroidism and those who form calcium-containing kidney stones.

Zinc can inhibit the absorption of certain antibiotics; take at least 2 hours apart to minimize interactions. Consult appropriate references for additional specific vitamin-drug interactions.

Information for Patients

Patients should be counseled to disclose all medical conditions, including use of all medications, vitamins and supplements, pregnancy, and breastfeeding.

Pediatric Use

Not recommended for pediatric use.

ADVERSE REACTIONS

Adverse reactions have been reported with specific vitamins and minerals, but generally at levels substantially higher than those in STROVITE® ONE.

DOSAGE AND ADMINISTRATION

One caplet daily or as directed by a physician.

HOW SUPPLIED

STROVITE® ONE is a white, oblong caplet, debossed EV0207; available in bottles of 90 caplets (0642-0207-90) and as professional samples (0642-0207-03).

STORAGE AND HANDLING

Storage conditions: Store at room temperature 15°-30°C (59°-86°F). Avoid excessive heat and moisture.

KEEP OUT OF REACH OF CHILDREN.

Rx

MANUFACTURED IN THE USA

Distributed by:
Exeltis USA, Inc.
Florham Park, NJ 07932
1-877-324-9349
www.exeltisusa.com
©2022 Exeltis USA, Inc. All rights reserved.

US PATENT NO. 6,863,904
STROVITE® ONE is a trademark of Exeltis Healthcare S.L.

Rev. 10/2022 2079003-04

PRINCIPAL DISPLAY PANEL - 90 Caplet Bottle Label

0642-0207-90

Strovite® ONE

IRON FREE

MULTIVITAMIN
AND
MINERAL SUPPLEMENT

GLUTEN AND LACTOSE FREE

90 Caplets

Rx